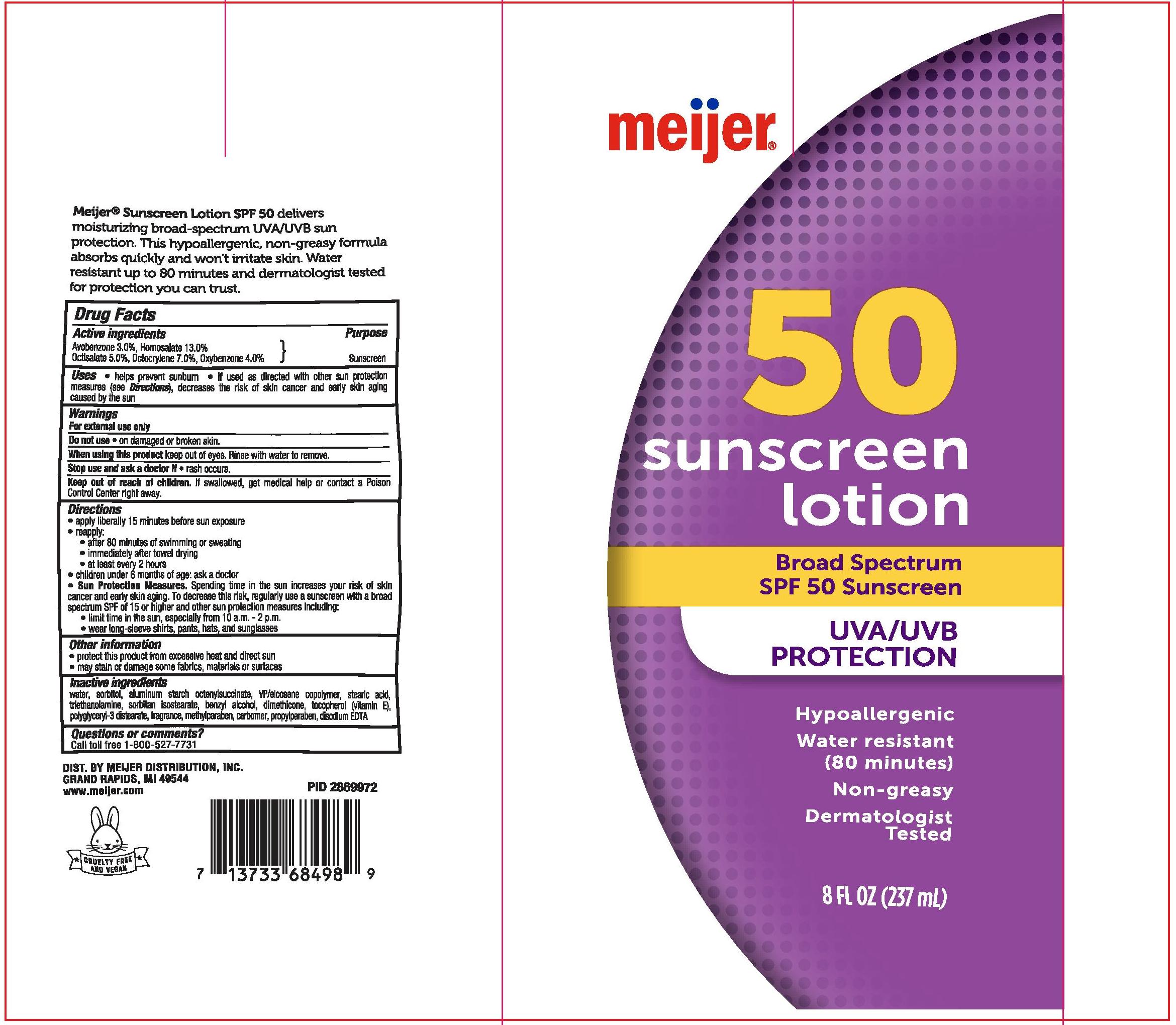 DRUG LABEL: MEIJER BROAD SPECTRUM SPF 50 SUNSCREEN
NDC: 41250-561 | Form: LOTION
Manufacturer: MEIJER DISTRIBUTION, INC.
Category: otc | Type: HUMAN OTC DRUG LABEL
Date: 20241016

ACTIVE INGREDIENTS: AVOBENZONE 30 mg/1 mL; HOMOSALATE 130 mg/1 mL; OCTISALATE 50 mg/1 mL; OCTOCRYLENE 70 mg/1 mL; OXYBENZONE 40 mg/1 mL
INACTIVE INGREDIENTS: METHYLPARABEN; WATER; SORBITOL; CARBOMER 934; STEARIC ACID; ALUMINUM STARCH OCTENYLSUCCINATE; POLYETHYLOXAZOLINE (200000 MW); DIMETHICONE; TOCOPHEROL; EDETATE DISODIUM; POLYGLYCERYL-3 DISTEARATE; PHENOXYETHANOL; ETHYLHEXYLGLYCERIN; SORBITAN ISOSTEARATE; BENZYL ALCOHOL; TROLAMINE; PROPYLPARABEN; EICOSYL POVIDONE

MEIJER BROAD SPECTRUM SPF 50 SUNSCREEN LOTION

Active ingredients

Avobenzone 3.0%

Homosalate 13.0%

Octisalate 5.0%

Octocrylene 7.0%

Oxybenzone 4.0%

Purpose

Sunscreen

Uses

• helps prevent sunburn

• if used as directed with other sun protection measures (see Directions), decreases the risk of skin cancer and early skin aging caused by the sun

Warnings

For external use only

Do not use • on damaged or broken skin.

When using this product • keep out of eyes. Rinse with water to remove

Stop use and ask a doctor if

• rash occurs.

Keep out of reach of children

If swallowed, get medical help or contact a Poison Control Center right away.

Directions

• apply liberally 15 minutes before sun exposure

• reapply:

• after 80 minutes of swimming or sweating

• immediately after towel drying

• at least every 2 hours

• children under 6 months of age: ask a doctor

• Sun Protection Measures. Spending time in the sun increases your risk of skin cancer and early skin aging. To decrease this risk,

regularly use a sunscreen with a broad-spectrum SPF of 15 or higher and other sun protection measures including:

• limit time in the sun, especially from 10 a.m. - 2 p.m.

• wear long-sleeve shirts, pants, hats, and sunglasses

Other information

• protect this product from excessive heat and direct sun

• may stain or damage some fabrics/materials or surfaces

Inactive ingredients

water, sorbitol, aluminum starch octenylsuccinate, VP/eicosene copolymer, stearic acid, triethanolamine, sorbitan isostearate, benzyl alcohol, dimethicone, tocopherol (vitamin E), polyglyceryl-3 distearate, fragrance, methylparaben, carbomer, propylparaben, disodium EDTA

Questions or comments?

Call toll free 1-800-527-7731

PACKAGE LABEL

MEIJER BROAD SPECTRUM SPF 50 SUNSCREEN LOTION

8 FL OZ (237mL)

NDC 41250-561-11